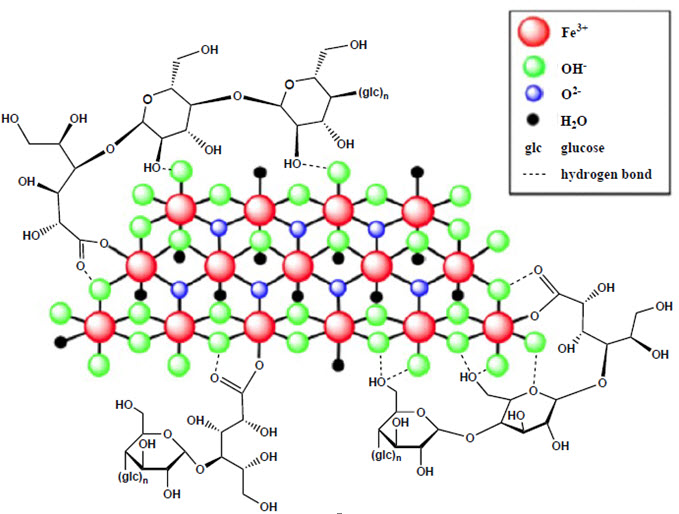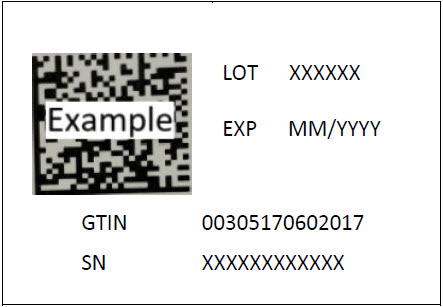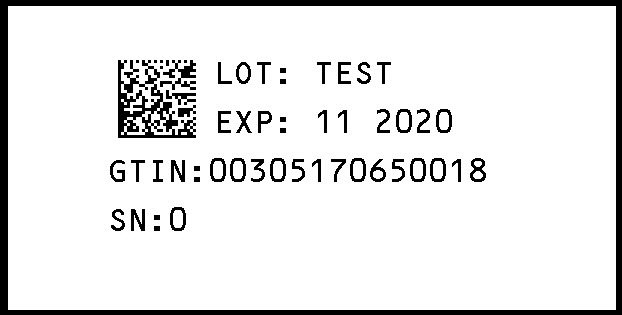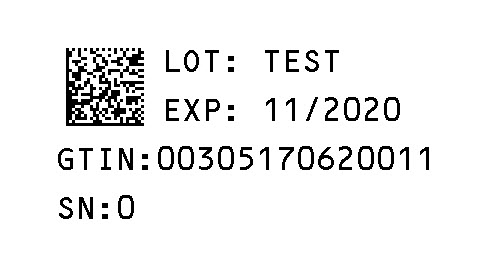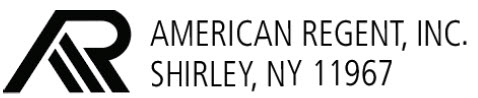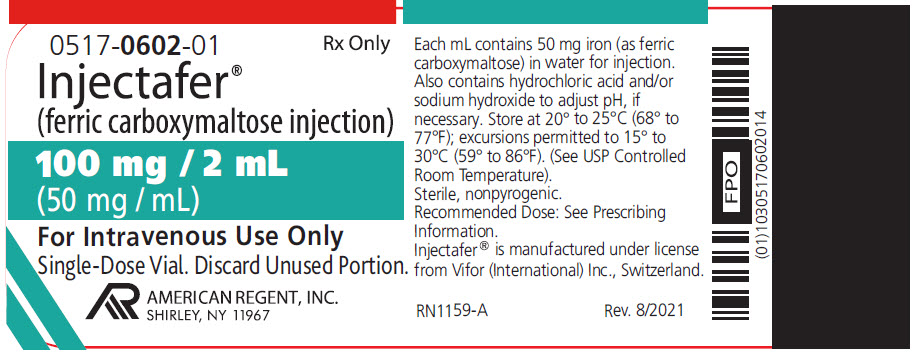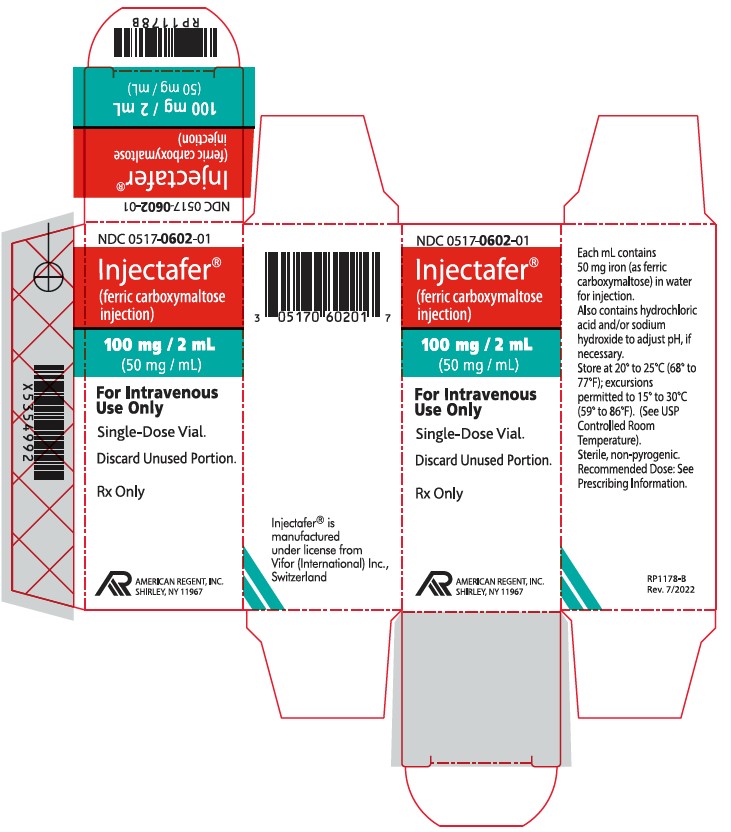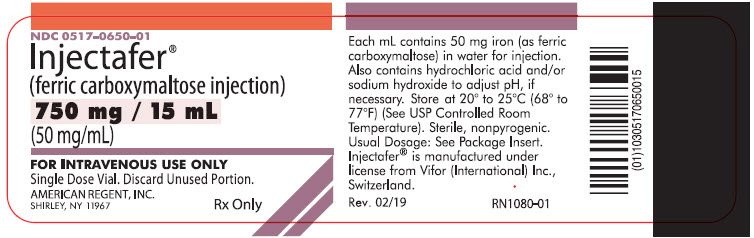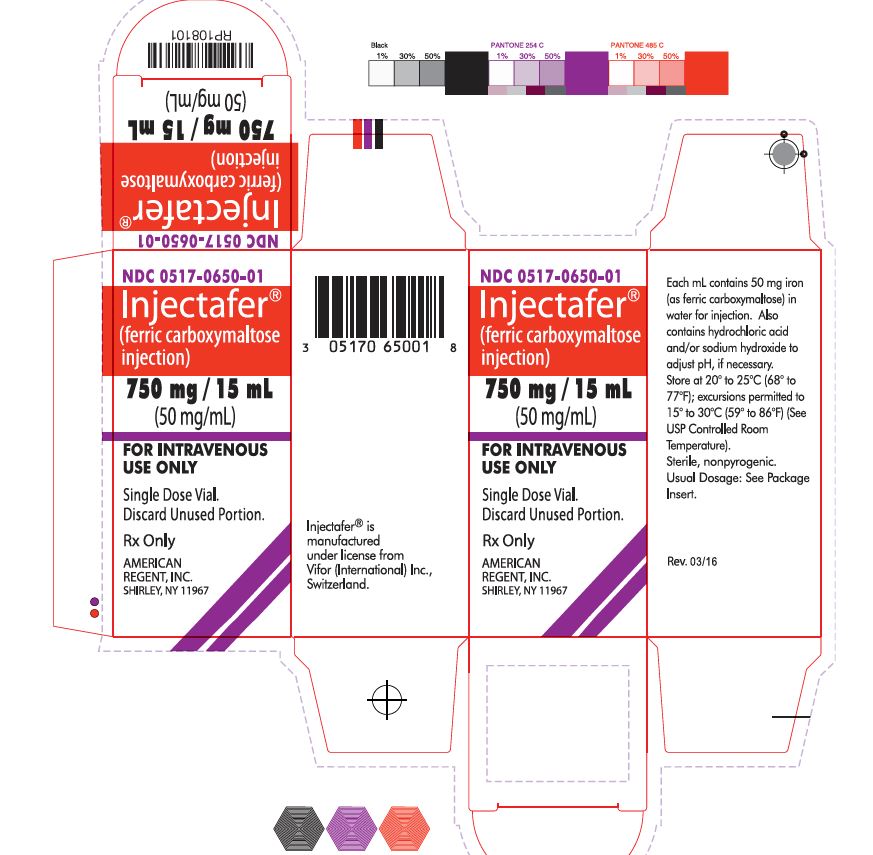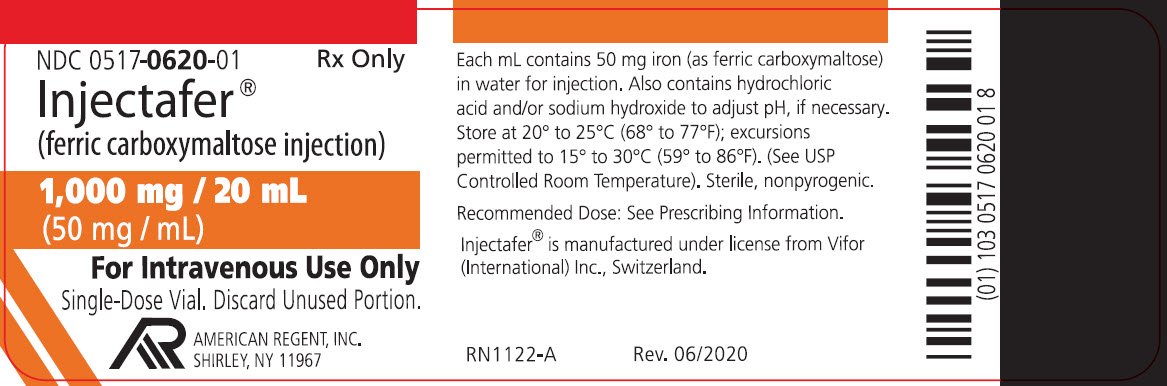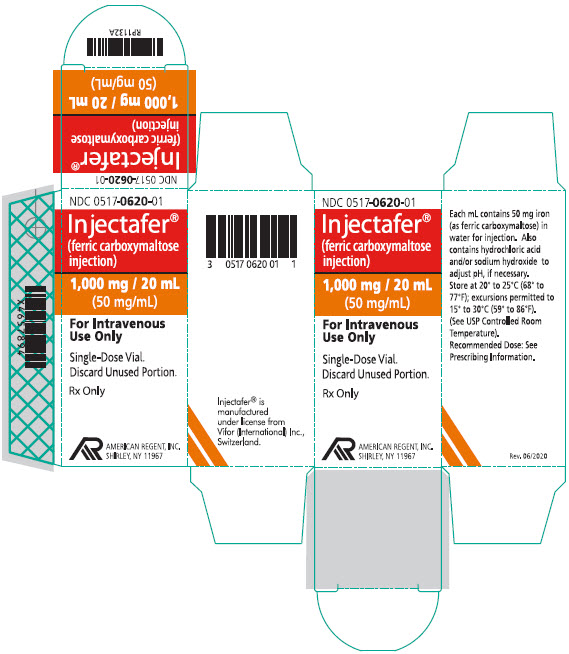 DRUG LABEL: Injectafer
NDC: 0517-0650 | Form: INJECTION, SOLUTION
Manufacturer: American Regent, Inc.
Category: prescription | Type: HUMAN PRESCRIPTION DRUG LABEL
Date: 20250101

ACTIVE INGREDIENTS: FERRIC CARBOXYMALTOSE 50 mg/1 mL

HIGHLIGHTS OF PRESCRIBING INFORMATION

These highlights do not include all the information needed to use Injectafer safely and effectively. See full prescribing information for Injectafer.
INJECTAFER® (ferric carboxymaltose injection), for intravenous use
Initial U.S. Approval: 2013

RECENT MAJOR CHANGES

Warnings and Precautions, Symptomatic Hypophosphatemia (5.2) 11/2024

1 INDICATIONS AND USAGE

Injectafer is an iron replacement product indicated for the treatment of:

• iron deficiency anemia (IDA) in:

- adult and pediatric patients 1 year of age and older who have either intolerance or an unsatisfactory response to oral iron. (1)
- adult patients who have non-dialysis dependent chronic kidney disease. (1)

• iron deficiency in adult patients with heart failure and New York Heart Association class II/III to improve exercise capacity. (1)

2 DOSAGE AND ADMINISTRATION

- For patients weighing 50 kg or more, the recommended dosage is Injectafer 750 mg intravenously in two doses separated by at least 7 days for a total cumulative dose of 1,500 mg of iron per course. For adult patients weighing 50 kg or more, an alternative dose of Injectafer 15 mg/kg body weight up to a maximum of 1,000 mg intravenously may be administered as a single-dose per course. (2.1)

- For patients weighing less than 50 kg, the recommended dosage is Injectafer 15 mg/kg body weight intravenously in two doses separated by at least 7 days per course. (2.1)

- See Section 2.1, Table 1 for dosage in patients with iron deficiency and heart failure. (2.1)

Injectafer treatment may be repeated if IDA or iron deficiency in heart failure reoccurs. (2.3)

3 DOSAGE FORMS AND STRENGTHS

Injection: 50 mg/mL

- 100 mg iron/2 mL single-dose vial
- 750 mg iron/15 mL single-dose vial
- 1,000 mg iron/20 mL single-dose vial

4 CONTRAINDICATIONS

Hypersensitivity to Injectafer or any of its inactive components.

5 WARNINGS AND PRECAUTIONS

- Hypersensitivity Reactions: Observe for signs and symptoms of hypersensitivity during and after Injectafer administration for at least 30 minutes and until clinically stable following completion of each administration. (5.1)
- Symptomatic Hypophosphatemia: Monitor serum phosphate levels in patients at risk for low serum phosphate who require a repeat course of treatment. (5.2)
- Hypertension: Monitor patients closely for signs and symptoms of hypertension following each Injectafer administration. (5.3)

6 ADVERSE REACTIONS

- The most common adverse reactions in adult patients (>2%) are nausea, hypertension, flushing, injection site reactions, erythema, hypophosphatemia, and dizziness. (6.1)

- The most common adverse reactions in pediatric patients (≥4%) are hypophosphatemia, injection site reactions, rash, headache, and vomiting. (6.1)

To report SUSPECTED ADVERSE REACTIONS, contact American Regent at 1-800-734-9236 or FDA at 1-800-FDA-1088 or www.fda.gov/medwatch.

8 USE IN SPECIFIC POPULATIONS

Pregnancy: Risk of hypersensitivity reactions which may have serious consequences for the fetus. (8.1)

FULL PRESCRIBING INFORMATION

RECENT MAJOR CHANGES

Warnings and Precautions, Symptomatic Hypophosphatemia. (5.2) 02/2020

1 INDICATIONS AND USAGE

Injectafer is indicated for the treatment of:

• iron deficiency anemia (IDA) in:

- adult and pediatric patients 1 year of age and older who have either intolerance or an unsatisfactory response to oral iron.
- adult patients who have non-dialysis dependent chronic kidney disease.

• iron deficiency in adult patients with heart failure and New York Heart Association class II/III to improve exercise capacity.

2 DOSAGE AND ADMINISTRATION

2.1 Recommended Dosage

Recommended Dosage for Treatment of Iron Deficiency Anemia

For patients weighing 50 kg or more, the recommended dosage is:

- Injectafer 750 mg intravenously in two doses separated by at least 7 days for a total cumulative dose of 1,500 mg of iron per course.
- In adult patients, Injectafer 15 mg/kg body weight up to a maximum of 1,000 mg intravenously may be administered as a single-dose per course.

For patients weighing less than 50 kg, the recommended dosage is Injectafer 15 mg/kg body weight intravenously in two doses separated by at least 7 days per course.

Recommended Dosage in Patients with Iron Deficiency with Heart Failure

See Table 1 for recommended dosage for treatment of iron deficiency in patients with heart failure and New York Heart Association class II/III to improve exercise capacity.
Table 1: Recommended Dosage in Patients with Iron Deficiency with Heart Failure

 | Weight less than 70 kg |  |  | Weight 70 kg or more
 | Hb (g/dL) |  |  | Hb (g/dL)
 | < 10 | 10 to 14 | > 14 to < 15 | < 10 | 10 to 14 | > 14 to < 15
Day 1 | 1,000 mg | 1,000 mg | 500 mg | 1,000 mg | 1,000 mg | 500 mg
Week 6 | 500 mg | No dose | No dose | 1,000 mg | 500 mg | No dose

Administer a maintenance dose of 500 mg at 12, 24 and 36 weeks if serum ferritin <100 ng/mL or serum ferritin 100-300 ng/mL with transferrin saturation <20%. There are no data available to guide dosing beyond 36 weeks or with Hb ≥15 g/dL.

2.2 Preparation and Administration

Administer Injectafer intravenously, either as an undiluted slow intravenous push or by infusion. When administered via infusion, dilute up to 1,000 mg of iron in no more than 250 mL of sterile 0.9% sodium chloride injection, USP, such that the concentration of the infusion is not less than 2 mg of iron per mL and administer over at least 15 minutes.

When added to an infusion bag containing 0.9% sodium chloride injection, USP, at concentrations ranging from 2 to 4 mg of iron per mL, Injectafer solution is physically and chemically stable for 72 hours when stored at room temperature. To maintain stability, do not dilute to concentrations less than 2 mg iron/mL.

Inspect parenteral drug products visually for the absence of particulate matter and discoloration prior to administration. The product contains no preservatives. Each vial of Injectafer is intended for a single dose.

When administering Injectafer 500 or 750 mg as a slow intravenous push, give at the rate of approximately 100 mg (2 mL) per minute. For Injectafer 1,000 mg, administer as a slow intravenous push over 15 minutes. Avoid extravasation of Injectafer since brown discoloration of the extravasation site may be long lasting. Monitor for extravasation. If extravasation occurs, discontinue the Injectafer administration at that site.

Discard unused portion.

2.3 Repeat Treatment Monitoring Safety Assessment

Injectafer treatment may be repeated if IDA or iron deficiency in heart failure reoccurs. Check serum phosphate levels in patients at risk for low serum phosphate who require a repeat course of treatment or for any patient who receives a repeat course of treatment within three months [see Warnings and Precautions (5.2)]. Treat hypophosphatemia as medically indicated.

3 DOSAGE FORMS AND STRENGTHS

Injection: 50 mg/mL, dark brown, non-transparent, sterile, aqueous solution.

- 100 mg iron/2 mL single-dose vial
- 750 mg iron/15 mL single-dose vial
- 1,000 mg iron/20 mL single-dose vial

4 CONTRAINDICATIONS

Injectafer is contraindicated in patients with a history of hypersensitivity to Injectafer or any of its components [see Warnings and Precautions (5.1)].

5 WARNINGS AND PRECAUTIONS

5.1 Hypersensitivity Reactions

Serious hypersensitivity reactions, including anaphylactic-type reactions, some of which have been life-threatening and fatal, have been reported in patients receiving Injectafer. Patients may present with shock, clinically significant hypotension, loss of consciousness, and/or collapse. Monitor patients for signs and symptoms of hypersensitivity during and after Injectafer administration for at least 30 minutes and until clinically stable following completion of the infusion. Only administer Injectafer when personnel and therapies are immediately available for the treatment of serious hypersensitivity reactions [see Adverse Reactions (6.1, 6.2)]. In clinical trials, serious anaphylactic/anaphylactoid reactions were reported in 0.1% (2/1,775) of subjects receiving Injectafer. Other serious or severe adverse reactions potentially associated with hypersensitivity which included, but not limited to, pruritus, rash, urticaria, wheezing, or hypotension were reported in 1.5% (26/1,775) of these subjects.

5.2 Symptomatic Hypophosphatemia

Symptomatic hypophosphatemia with serious outcomes including osteomalacia and fractures requiring clinical intervention has been reported in patients treated with Injectafer in the post-marketing setting. These cases have occurred mostly after repeated exposure to Injectafer in patients with no reported history of renal impairment. However, symptomatic hypophosphatemia has been reported after one dose. Possible risk factors for hypophosphatemia include a history of gastrointestinal disorders associated with malabsorption of fat-soluble vitamins or phosphate, inflammatory bowel disease, concurrent or prior use of medications that affect proximal renal tubular function, hyperparathyroidism, vitamin D deficiency, malnutrition, and hereditary hemorrhagic telangiectasia (HHT or Osler-Weber-Rendu syndrome). In most cases, hypophosphatemia resolved within three months.

Correct pre-existing hypophosphatemia prior to initiating therapy with Injectafer. Monitor serum phosphate levels in patients at risk for chronic low serum phosphate. Check serum phosphate levels prior to a repeat course of treatment in patients at risk for low serum phosphate and in any patient who receives a second course of therapy within three months [see Dosage and Administration (2.3)]. Treat hypophosphatemia as medically indicated.

5.3 Hypertension

In clinical studies, hypertension was reported in 4% (67/1,775) of subjects in clinical trials 1 and 2. Transient elevations in systolic blood pressure, sometimes occurring with facial flushing, dizziness, or nausea were observed in 6% (106/1,775) of subjects in these two clinical trials. These elevations generally occurred immediately after dosing and resolved within 30 minutes. Monitor patients for signs and symptoms of hypertension following each Injectafer administration [see Dosage and Administration (2)].

5.4 Laboratory Test Alterations

In the 24 hours following administration of Injectafer, laboratory assays may overestimate serum iron and transferrin bound iron by also measuring the iron in Injectafer.

6 ADVERSE REACTIONS

The following clinically significant adverse reactions are discussed in greater detail in other sections of the labeling:

- Hypersensitivity Reactions [see Warnings and Precautions (5.1)]
- Hypophosphatemia [see Warnings and Precautions (5.2)]
- Hypertension [see Warnings and Precautions (5.3)]
- Laboratory Test Alterations [see Warnings and Precautions (5.4)]

6.1 Clinical Trials Experience

Because clinical trials are conducted under widely varying conditions, the adverse reaction rates observed cannot be directly compared to rates in other clinical trials and may not reflect the rates observed in clinical practice.

Adults
In two randomized clinical studies [Studies 1 and 2, see Clinical Studies (14)], a total of 1,775 patients were exposed to Injectafer 15 mg/kg body weight up to a maximum single dose of 750 mg of iron on two occasions separated by at least 7 days up to a cumulative dose of 1,500 mg of iron.

Adverse reactions reported by ≥1% of treated patients are shown in the following table.

Table 2. Adverse reactions reported in ≥1% of Study Patients in Clinical Trials 1 and 2

 | Injectafer; (N=1,775) % | Pooled Comparatorsa (N=1,783) % | Oral iron (N=253) %
Nausea | 7.2 | 2 | 1.2
Hypertension* | 4 | 2 | 0.4
Flushing* | 4 | 0.2 | 0
Injection site reactions* | 3 | 3.2 | 0
Erythema* | 3 | 0.6 | 0
Hypophosphatemia | 2.1 | 0.1 | 0
Dizziness* | 2.1 | 1.3 | 0.4
Vomiting | 2 | 1 | 0.4
Injection Site Discoloration** | 1.4 | 0.3 | 0
Headache* | 1.3 | 1.2 | 0.4
Hepatic enzyme increased* | 1.2 | 0.2 | 0
Dysgeusia* | 1.2 | 2.1 | 0
Hypotension | 1 | 2 | 0
Rash* | 1 | 0.3 | 0
Constipation | 0.5 | 0.9 | 3.2

a Includes oral iron and all formulations of IV iron other than Injectafer
*Grouped Terms:
Hypertension includes hypertension, blood pressure increased, and hypertensive crisis.

Flushing includes flushing and hot flush.

Injection site reactions include injection site extravasation, injection site discoloration, injection site pain, injection site irritation, injection site bruising, injection site reaction, injection site discomfort, injection site erythema, injection site hematoma, injection site hemorrhage, injection site pruritus, injection site rash, and injection site swelling.

Erythema includes erythema and injection site erythema.

Dizziness includes dizziness, balance disorder, and vertigo.

**Injection site discoloration was also included in the injection site local administration reactions grouped term.

Headache includes headache and migraine.

Hepatic enzyme increased includes alanine aminotransferase increased and aspartate aminotransferase increased.

Dysgeusia includes dysgeusia and ageusia.

Rash includes rash, urticaria, skin exfoliation, blister, erythema multiforme, injection site rash, rash maculo-papular, and rash pruritic.

Other adverse reactions reported by ≥0.5% of treated patients include abdominal pain, diarrhea, gamma glutamyl transferase increased, paresthesia, and sneezing. Transient decreases in laboratory blood phosphorus levels (< 2 mg/dL) have been observed in 27% (440/1,638) of patients in clinical trials.
Pooled data from two Phase 3 studies 1VIT09030 (NCT00981045) and 1VIT09031 (NCT00982007) with a dosing regimen of Injectafer 15 mg/kg up to a maximum of 750 mg x 2 doses to a cumulative dose of 1,500 mg of iron were analyzed to compare rates of adverse reactions in two Phase 3 parallel group studies 1VIT07017 (NCT00548860) and 1VIT07018 (NCT00548691) with a dosing regimen of Injectafer 15 mg/kg up to a maximum of 1,000 mg single dose (Table 3).

Table 3. Adverse Reactions (≥1% in any Treatment Group) In Patients Receiving Two Doses of 15 mg/kg to a Maximum of 750 mg to a Cumulative Dose of 1,500 mg or a Single Dose of Injectafer 15 mg/kg to a Maximum of 1,000 mg.

 | Injectafer 15 mg/kg to a maximum of 750 mg x 2 doses to a cumulative dose of 1,500 mg | Injectafer 15 mg/kg to a maximum of 1,000 mg; single dose
 | IVIT09030 and IVIT09031b (N=1,775); % | IVIT07017 and IVIT07018a(N=1,200); %
Any Adverse Reaction | 24 | 12
Injection site reactions* | 3 | 4
Injection site extravasation** | 0.2 | 2
Hepatic enzyme increased* | 1.2 | 1.2
Rash* | 1 | 1.2
Headache* | 1.3 | 1
Dizziness* | 2.1 | 1
Dysgeusia* | 1.2 | 1
Nausea | 7.2 | 1
Hypertension* | 4 | 1
Hypophosphatemia | 2.1 | 1
Erythema* | 3 | 0.3
Flushing* | 4 | 0.3
Vomiting | 2 | 0.2
Injection site discoloration** | 1.4 | <0.1
Hypotension | 1 | <0.1

ab Included studies 1VIT07017, 1VIT07018, 1VIT09030 and 1VIT09031

*Grouped Terms

**Injection site extravasation and injection site discoloration were also included in the injection site reactions grouped term.
Pediatric Patients
The safety of Injectafer in pediatric patients was evaluated in study 1VIT17044 (NCT03523117; Study 3). Study 1VIT17044 was a randomized, active-controlled study in which 40 patients (1 to 12 years of age: 10 patients, 12 to 17 years of age: 30 patients) received Injectafer 15 mg/kg to a maximum single dose of 750 mg (whichever was smaller) on Days 0 and 7 for a maximum total dose of 1,500 mg; 38 patients evaluable for safety in the control arm received an age-dependent formulation of oral ferrous sulfate for 28 days. The median age of patients who received Injectafer was 14.5 years (range, 1-17); 83% were female; 88% White and 13% Black. The most common adverse reactions (≥4%) were hypophosphatemia, injection site reactions, rash, headache, and vomiting.
Table 4 summarizes the adverse reactions in Study 3.
Table 4. Adverse Reactions of any Grade in Pediatric Patients Receiving Injectafer in Study 3

 | Injectafer (N=40) % | Oral Ferrous Sulfate (N=38) %
Any Adverse Reactions | 35 | 26
Hypophosphatemia* | 13 | 0
Injection site reactions* | 8 | 0
Rash* | 8 | 0
Headache | 5 | 3
Vomiting | 5 | 3
Nasopharyngitis | 3 | 5
Flushing | 3 | 0
Gastrointestinal infections | 3 | 0
Liver function test increased | 3 | 0
Platelet count decreased | 3 | 0
White blood cell count decreased | 3 | 0

*Grouped Terms
Injection site reactions include infusion site hematoma, infusion site hypoesthesia and injection site pain.
Hypophosphatemia includes hypophosphatemia and blood phosphorus decreased.
Rash includes rash, exanthema and urticaria.

Patients with Iron Deficiency and Heart Failure

The safety of Injectafer was evaluated in adult patients with iron deficiency and heart failure in randomized controlled trials FAIR-HF (NCT00520780), CONFIRM-HF (NCT01453608) and AFFIRM-AHF (NCT02937454) in which 1,016 patients received Injectafer versus 857 received placebo. The overall safety profile of Injectafer was consistent across the studied indications.

6.2 Post-marketing Experience

The following adverse reactions have been identified during post approval use of Injectafer. Because these reactions are reported voluntarily from a population of uncertain size, it is not always possible to reliably estimate their frequency or establish a causal relationship to drug exposure.

The following adverse reactions have been reported from the post-marketing spontaneous reports with Injectafer:

- Cardiac disorders: Tachycardia
- General disorders and administration site conditions: Chest discomfort, chills, pyrexia
- Metabolism and nutrition disorders: Hypophosphatemia
- Musculoskeletal and connective tissue disorders: Arthralgia, back pain, hypophosphatemic osteomalacia
- Nervous system disorders: Syncope
- Respiratory, thoracic and mediastinal disorders: Dyspnea
- Skin and subcutaneous tissue disorders: Angioedema, erythema, pruritus, urticaria
- Pregnancy: Fetal bradycardia

8 USE IN SPECIFIC POPULATIONS

8.1 Pregnancy

Risk Summary

Parenteral iron administration may be associated with hypersensitivity reactions [see Warnings and Precautions (5.1)], which may have serious consequences, such as fetal bradycardia (see Clinical Considerations). Advise pregnant women of the potential risk to a fetus. Published studies and available data from postmarketing reports with intravenous Injectafer are insufficient to assess the risk of major birth defects and miscarriage.
There are risks to the mother and fetus associated with untreated IDA in pregnancy as well as risks to the fetus associated with maternal severe hypersensitivity reactions (see Clinical Considerations).

In animal reproduction studies, administration of ferric carboxymaltose to rabbits during the period of organogenesis caused adverse developmental outcomes including fetal malformations and increased implantation loss at maternally toxic doses of approximately 12% to 23% of the human weekly dose of 750 mg (based on body surface area).

The estimated background risk of major birth defects and miscarriage for the indicated populations is unknown. All pregnancies have a background risk of birth defect, loss, or other adverse outcomes. In the U.S. general population, the estimated background risk of major birth defects and miscarriage in clinically recognized pregnancies is 2% to 4% and 15% to 20%, respectively.

Clinical Considerations
Disease-associated maternal and/or embryo/fetal risk
Untreated IDA in pregnancy is associated with adverse maternal outcomes such as post-partum anemia. Adverse pregnancy outcomes associated with IDA include increased risk for preterm delivery and low birth weight.
Fetal/Neonatal adverse reactions

Severe adverse reactions including circulatory failure (severe hypotension, shock including in the context of anaphylactic reaction) may occur in pregnant women with parenteral iron products (such as Injectafer) which may cause fetal bradycardia, especially during the second and third trimester.

Data
Human Data

Published data from randomized controlled studies, prospective observational studies and retrospective studies on the use of ferric carboxymaltose in pregnant women have not reported an association with intravenous ferric carboxymaltose and major birth defects and miscarriage. However, these studies cannot establish or exclude the absence of any drug-related risk during pregnancy.

Animal Data

Administration of ferric carboxymaltose to rats as a one-hour intravenous infusion up to 30 mg/kg/day iron on gestation days 6 to 17 did not result in adverse embryonic or fetal findings. This daily dose in rats is approximately 40% of the human weekly dose of 750 mg based on body surface area. In rabbits, ferric carboxymaltose was administered as a one-hour infusion on gestation days 6 to 19 at iron doses of 4.5, 9, 13.5, and 18 mg/kg/day. Malformations were seen starting at the daily dose of 9 mg/kg (23% of the human weekly dose of 750 mg). Spontaneous abortions occurred starting at the daily iron dose of 4.5 mg/kg (12% of the human weekly dose of 750 mg based on body surface area). Pre-implantation loss was at the highest dose. Adverse embryonic or fetal effects were observed in the presence of maternal toxicity.

A pre- and post-natal development study was conducted in rats at intravenous doses up to 18 mg/kg/day of iron (approximately 23% of the weekly human dose of 750 mg based on body surface area). There were no adverse effects on survival of offspring, their behavior, sexual maturation or reproductive parameters.

8.2 Lactation

Risk Summary

The available published data on the use of ferric carboxymaltose in lactating women demonstrate that iron is present in breast milk. Among the breastfed infants, adverse reactions included constipation and diarrhea but none of the adverse reactions reported were considered related to ferric carboxymaltose exposure through breastmilk. There is no information on the effects of ferric carboxymaltose on milk production. The developmental and health benefits of breastfeeding should be considered along with the mother’s clinical need for Injectafer in addition to any potential adverse effects on the breastfed child from the drug or from the underlying maternal condition.

8.4 Pediatric Use

The safety and effectiveness of Injectafer for IDA in pediatric patients aged 1 year and older who have normal kidney function and have either intolerance to oral iron or have had unsatisfactory response to oral iron have been established. Use of Injectafer for this indication in this age group is supported by evidence from adequate and well-controlled studies of Injectafer in adults with additional pharmacodynamic and safety data in pediatric patients aged 1 year and older [see Adverse Reactions (6.1) and Clinical Pharmacology (12.3)].
Safety and effectiveness of Injectafer have not been established in pediatric patients less than 1 year of age with IDA.

Safety and effectiveness of Injectafer have not been established to improve exercise capacity in pediatric patients with ID and symptomatic heart failure.

8.5 Geriatric Use

Of the 1,775 subjects in clinical studies of Injectafer, 50% were 65 years and over, while 25% were 75 years and over. No overall differences in safety or effectiveness were observed between these subjects and younger subjects, and other reported clinical experience has not identified differences in responses between the elderly and younger patients, but greater sensitivity of some older individuals cannot be ruled out.

10 OVERDOSAGE

Excessive dosages of Injectafer may lead to accumulation of iron in storage sites potentially leading to hemosiderosis. A patient who received Injectafer 18,000 mg over 6 months developed hemosiderosis with multiple joint disorder, walking disability, and asthenia. In the postmarketing setting, hypophosphatemic osteomalacia has been reported in patients who have received repeated high-cumulative courses of Injectafer.

11 DESCRIPTION

Ferric carboxymaltose, an iron replacement product, is an iron carbohydrate complex with the chemical name of polynuclear iron (III)-hydroxide 4(R)-(poly-(1→4)-O-α-D-glucopyranosyl)-oxy-2(R),3(R),5(R),6-tetrahydroxy-hexanoate. It has a relative molecular weight of approximately 150,000 Da corresponding to the following empirical formula:

[FeOx(OH)y(H2O)z]n [{(C6H10O5)m (C6H12O7)}l]k,

where n ≈ 10^3, m ≈ 8, l ≈ 11, and k ≈ 4
(l represents the mean branching degree of the ligand).

The chemical structure is presented below:

Injectafer (ferric carboxymaltose injection) is a dark brown, sterile, aqueous, isotonic colloidal solution for intravenous injection. Each mL contains 50 mg iron as ferric carboxymaltose in water for injection. Injectafer is available in 2 mL, 15 mL and 20 mL single-dose vials. Sodium hydroxide and/or hydrochloric acid may have been added to adjust the pH to 5.0-7.0.

Vial closure is not made with natural rubber latex.

12 CLINICAL PHARMACOLOGY

12.1 Mechanism of Action

Ferric carboxymaltose is a colloidal iron (III) hydroxide in complex with carboxymaltose, a carbohydrate polymer that releases iron.

12.2 Pharmacodynamics

Using positron emission tomography (PET) it was demonstrated that red cell uptake of ^59Fe and ^52Fe from Injectafer ranged from 61% to 99%. In patients with iron deficiency, red cell uptake of radiolabeled iron ranged from 91% to 99% at 24 days after Injectafer dose. In patients with renal anemia, red cell uptake of radiolabeled iron ranged from 61% to 84% at 24 days after Injectafer dose.

12.3 Pharmacokinetics

After administration of a single dose of Injectafer of 100 to 1,000 mg of iron in iron deficient adult patients, maximum iron concentration of 37 µg/mL to 333 µg/mL were obtained respectively after 15 minutes to 1.21 hours post dose. The volume of distribution was estimated to be 3 L.

The iron injected or infused was rapidly cleared from the plasma, the terminal half-life ranged from 7 to 12 hours. Renal elimination of iron was negligible.
After administration of a single dose of Injectafer 15 mg/kg in pediatric patients 1-17 years of age, the maximum concentrations ranged between 124 and 418.1 μg/mL and the median time to maximum concentration was 7 minutes. The elimination half-life of Injectafer in pediatric patients was approximately 9.7 hours. The total median 72-hour exposure (AUC0-72h) after a single dose of Injectafer 15 mg/kg in pediatric patients was 4,529.7 μg∙h/mL while the median exposure after a single dose of 1,000 mg in adults was 5,875.3 μg∙h/mL.

13 NONCLINICAL TOXICOLOGY

13.1 Carcinogenesis, Mutagenesis, and Impairment of Fertility

Carcinogenicity studies have not been performed with ferric carboxymaltose.

Ferric carboxymaltose was not genotoxic in the following genetic toxicology studies: in vitro microbial mutagenesis (Ames) assay, in vitro chromosome aberration test in human lymphocytes, in vitro mammalian cell mutation assay in mouse lymphoma L5178Y/TK+/- cells, in vivo mouse micronucleus test at single intravenous doses up to 500 mg/kg.

In a combined male and female fertility study, ferric carboxymaltose was administered intravenously over one hour to male and female rats at iron doses of up to 30 mg/kg. Animals were dosed 3 times per week (on Days 0, 3, and 7). There was no effect on mating function, fertility or early embryonic development. Based on body surface area, the dose of 30 mg/kg in animals is approximately 40% of the human dose of 750 mg.

14 CLINICAL STUDIES

14.1 Iron Deficiency Anemia

The safety and efficacy of Injectafer for treatment of IDA were evaluated in two randomized, open-label, controlled clinical trials (Trial 1 and Trial 2). In these two trials, Injectafer was administered at a dose of 15 mg/kg body weight up to a maximum single dose of 750 mg of iron on two occasions separated by at least 7 days up to a cumulative dose of 1,500 mg of iron.

Trial 1: Iron Deficiency Anemia in Patients Who Are Intolerant to Oral Iron or Have Had Unsatisfactory Response to Oral Iron

Trial 1: A Multi-center, Randomized, Active Controlled Study to Investigate the Efficacy and Safety of Intravenous Ferric Carboxymaltose (FCM) in Patients with Iron Deficiency Anemia (IDA), (NCT00982007) was a randomized, open-label, controlled clinical study in patients with IDA who had an unsatisfactory response to oral iron (Cohort 1) or who were intolerant to oral iron (Cohort 2) during the 14-day oral iron run-in period. Inclusion criteria prior to randomization included hemoglobin (Hb) <12 g/dL, ferritin ≤100 ng/mL or ferritin ≤300 ng/mL when transferrin saturation (TSAT) ≤30%. Cohort 1 subjects were randomized to Injectafer or oral iron for 14 more days. Cohort 2 subjects were randomized to Injectafer or another IV iron per standard of care [90% of subjects received iron sucrose]. The mean age of study patients was 43 years (range, 18 to 94); 94% were female; 42% were Caucasian, 32% were African American, 24% were Hispanic, and 2% were other races. The primary etiologies of IDA were heavy uterine bleeding (47%) and gastrointestinal disorders (17%).

Table 5 shows the baseline and the change in hemoglobin from baseline to highest value between baseline and Day 35 or time of intervention.

Table 5. Mean Change in Hemoglobin From Baseline to the Highest Value Between Day 35 or Time of Intervention (Modified Intent‑to‑Treat Population)

Hemoglobin (g/dL); Mean (SD) | Cohort 1 |  | Cohort 2
Hemoglobin (g/dL); Mean (SD) | Injectafer (N=244) | Oral Iron (N=251) | Injectafer (N=245) | IV SCa (N=237)
Baseline | 10.6 (1.0) | 10.6 (1.0) | 9.1 (1.6) | 9.0 (1.5)
Highest Value | 12.2 (1.1) | 11.4 (1.2) | 12.0 (1.2) | 11.2 (1.3)
Change (from baseline to highest value) | 1.6 (1.2) | 0.8 (0.8) | 2.9 (1.6) | 2.2 (1.3)
p-value | 0.001 |  | 0.001

SD=standard deviation; aIntravenous iron per standard of care

Increases from baseline in mean ferritin (264.2 ± 224.2 ng/mL in Cohort 1 and 218.2 ± 211.4 ng/mL in Cohort 2), and transferrin saturation (13 ± 16% in Cohort 1 and 20 ± 15% in Cohort 2) were observed at Day 35 in Injectafer-treated patients.

Trial 2: Iron Deficiency Anemia in Patients with Non-Dialysis Dependent Chronic Kidney Disease

Trial 2: REPAIR-IDA, Randomized Evaluation of efficacy and safety of Ferric Carboxymaltose in Patients with Iron Deficiency Anemia and Impaired Renal function, (NCT00981045) was a randomized, open-label, controlled clinical study in patients with non-dialysis dependent chronic kidney disease. Inclusion criteria included hemoglobin (Hb) ≤11.5 g/dL, ferritin ≤ 100 ng/mL or ferritin ≤300 ng/mL when transferrin saturation (TSAT) ≤ 30%. Study patients were randomized to either Injectafer or Venofer. The mean age of study patients was 67 years (range, 19 to 101); 64% were female; 54% were Caucasian, 26% were African American, 18% Hispanics, and 2% were other races.

Table 6 shows the baseline and the change in hemoglobin from baseline to highest value between baseline and Day 56 or time of intervention.

Table 6. Mean Change in Hemoglobin From Baseline to the Highest Value Between Baseline and Day 56 or Time of Intervention (Modified Intent‑to‑Treat Population)

Hemoglobin (g/dL) Mean (SD) | Injectafer (N=1,249) | Venofer (N=1,244)
Baseline | 10.3 (0.8) | 10.3 (0.8)
Highest Value | 11.4 (1.2) | 11.3 (1.1)
Change (from baseline to highest value) | 1.1 (1.0) | 0.9 (0.92)
Treatment Difference (95% CI) | 0.21 (0.13, 0.28)

Increases from baseline in mean ferritin (734.7 ± 337.8 ng/mL) and transferrin saturation (30 ± 17%) were observed prior to Day 56 in Injectafer-treated patients.

14.2 Iron Deficiency in Heart Failure

Trial 3: FER-CARS-05 (CONFIRM-HF) was a randomized, double-blind, placebo-controlled, study in patients with iron deficiency and chronic heart failure with left ventricular ejection fraction of < 45% and New York Heart Association (NYHA) class II/III to determine whether intravenous Injectafer improves exercise capacity measured as change from baseline to 24 weeks in 6-minute walk distance (6MWD).

Iron deficiency was defined as serum ferritin <100 ng/mL or 100 to 300 ng/mL with TSAT <20%. Patients with Hb of ≥ 15 g/dl were excluded. Of the 304 patients, 150 were randomized to Injectafer and 151 to placebo. The median age of study patients was 71 years (range, 35 to 88); 46% were female; 99% were Caucasian.

At baseline, mean (SD) Hb was 12 g/dl (1.4), ferritin 57 ng/ml (45), TSAT 19 % (13.7), LVEF 37% (7), brain natriuretic peptide 770 pg/mL (973); and 57 and 43% were classified as NYHA class II and III, respectively.

At baseline, 95% of patients were treated with angiotensin converting enzyme inhibitor (ACEi) or angiotensin receptor blocker (ARB), 91% with beta-blocker, 59% with aldosterone antagonists, and 90% with diuretic.

The mean change in 6MWD from Baseline to Week 24 in Injectafer-treated patients was 18 meters (95% CI 4, 32), and placebo-treated patients was -7 meters (95% CI -21, 7), with between group difference of 25 meters (7, 43), p-value 0.007, favoring Injectafer. Results were generally similar within age and sex subgroups.

In Injectafer-treated patients, change from Baseline to Week 24 in serum ferritin was 269 ng/mL (229, 309), in TSAT was 9% (7, 11), and in Hb was 0.6 g/dL (0.3, 0.8).

16 HOW SUPPLIED/STORAGE AND HANDLING

Injectafer (ferric carboxymaltose injection) is a dark brown, non-transparent, sterile, aqueous solution.

NDC 0517-0602-01 100 mg iron/2 mL Single-Dose Vial Individually Boxed

NDC 0517-0650-01 750 mg iron/15 mL Single-Dose Vial Individually Boxed

NDC 0517-0620-01 1,000 mg iron/20 mL Single-Dose Vial Individually Boxed
Store at 20°C to 25°C (68°F to 77°F); excursions permitted to 15°C to 30°C (59°F to 86°F). [See the USP controlled room temperature.] Do not freeze.

17 PATIENT COUNSELING INFORMATION

Advise the patient to read the FDA-approved patient labeling (Patient Information) and discuss with the patient the etiology of the iron deficiency anemia and the patient’s iron deficiency anemia treatment options.
Prior History of Reactions to Parenteral Iron Products
Question patients regarding any prior history of reactions to parenteral iron products [see Warnings and Precautions (5.1)].

Serious Hypersensitivity Reactions
Advise patients to report any signs and symptoms of hypersensitivity that may develop during and following Injectafer administration, such as rash, itching, dizziness, lightheadedness, swelling, and breathing problems [see Warnings and Precautions (5.1)].

Symptomatic Hypophosphatemia

Advise patients to report any signs or symptoms of hypophosphatemia such as fatigue, muscle weakness or pain, bone and joint pain, or bone fractures [see Warnings and Precautions (5.2)].

Pregnancy
Advise pregnant women about the risk of hypersensitivity reactions which may have serious consequences for the fetus. Advise patients who may become pregnant to inform their healthcare provider of a known or suspected pregnancy [see Use in Specific Populations (8.1)].

Injectafer is manufactured under license from Vifor (International) Inc, Switzerland.

Distributed by:

RQ1052-I

Patient Information

INJECTAFER (in-jekt-a-fer)

(ferric carboxymaltose injection)

What is INJECTAFER?

INJECTAFER is a prescription iron replacement medicine used for the treatment of:

- iron deficiency anemia (IDA) in:

- adults and children 1 year of age and older who cannot tolerate iron taken by mouth (oral) or who have not responded well to oral iron.
- adults who have chronic kidney disease who are not on dialysis (non-dialysis dependent chronic kidney disease).

- iron deficiency in adults with mild to moderate heart failure to improve the ability to exercise (improve exercise capacity).

It is not known if INJECTAFER is safe and effective in children with IDA who are under 1 year of age.

It is not known if INJECTAFER is safe and effective in children with iron deficiency and mild to moderate heart failure to improve exercise capacity.

Do not receive INJECTAFER.

Do not receive INJECTAFER if you are allergic to ferric carboxymaltose or any of the ingredients in INJECTAFER. See the end of this Patient Information leaflet for a complete list of ingredients in INJECTAFER.

Before receiving INJECTAFER, tell your healthcare provider about all of your medical conditions, including if you:

- have had an allergic reaction to iron given into your vein
- have a history of trouble absorbing certain vitamins or phosphate in your body
- have inflammatory bowel disease
- have hyperparathyroidism
- have low vitamin D levels
- have high blood pressure
- have previously received INJECTAFER
- are pregnant or plan to become pregnant. INJECTAFER may harm your unborn baby. Tell your healthcare provider right away if you become pregnant or think you are pregnant during treatment with INJECTAFER.
- are breastfeeding or plan to breastfeed. INJECTAFER passes into your breast milk. It is not known if INJECTAFER will harm your baby. Talk to your healthcare provider about the best way to feed your baby during treatment with INJECTAFER.

Tell your healthcare provider about all the medicines you take, including prescription and over-the-counter medicines, vitamins, and herbal supplements.

How will I receive INJECTAFER?

- INJECTAFER is given into your vein (intravenously) by your healthcare provider.
- INJECTAFER is usually given in 2 doses at least 7 days apart for IDA, or 6 weeks apart for iron deficiency with mild to moderate heart failure to improve exercise capacity.
- If your healthcare provider decides it is right for you, INJECTAFER may be given intravenously by your healthcare provider as a single-dose treatment.
- INJECTAFER treatment may be repeated if your healthcare provider decides it is needed.
  What are the possible side effects of INJECTAFER?
  INJECTAFER may cause serious side effects, including:

- Allergic reactions. Serious life-threatening allergic reactions that can lead to death have happened in people who receive INJECTAFER and may include the following signs or symptoms:

- low blood pressure
- feeling dizzy or lightheaded
- loss of consciousness
- trouble breathing
- swelling
- fast heartbeat
- cold or clammy skin
- feet or hands turn blue
- itching
- rash
- hives
- wheezing
  Your healthcare provider will watch you during and for at least 30 minutes after you receive INJECTAFER. Tell your healthcare provider right away if you develop any signs or symptoms of allergic reactions during or after treatment with INJECTAFER.

- Symptoms of low blood phosphate levels. INJECTAFER may cause low levels of phosphate in your blood that may be serious and can lead to softening of your bones and broken bones (fractures), especially in people who have received multiple INJECTAFER treatments. Your healthcare provider may check your blood phosphate levels before a repeat treatment with INJECTAFER if you are at risk for low blood phosphate levels. If a repeat treatment is needed within 3 months of your last treatment your healthcare provider should check your blood phosphate levels.
  Tell your healthcare provider if you develop any of the following signs or symptoms of low blood phosphate levels during treatment with INJECTAFER:

- feeling very tired
- muscle weakness or pain
- bone or joint pain
- broken bones
  • High blood pressure. High blood pressure, sometimes with redness and warmth of the face (facial flushing), dizziness, or nausea, has happened during treatment with INJECTAFER. Your healthcare provider will check your blood pressure and check for any signs and symptoms of high blood pressure after you receive INJECTAFER.
  The most common side effects of INJECTAFER in adults include:

- nausea
- high blood pressure
- flushing
- injection site reactions
- skin redness
- low levels of phosphate in your blood
- dizziness

The most common side effects of INJECTAFER in children include:

- low levels of phosphate in your blood
- injection site reactions
- rash
- headache
- vomiting

These are not all the possible side effects of INJECTAFER.

Call your doctor for medical advice about side effects. You may report side effects to FDA at 1-800-FDA-1088.

General information about the safe and effective use of INJECTAFER.

Medicines are sometimes prescribed for purposes other than those listed in a Patient Information leaflet. You can ask your pharmacist or healthcare provider for information about INJECTAFER that is written for health professionals.

What are the ingredients in INJECTAFER?

Active ingredient: ferric carboxymaltose.

Inactive ingredients: water for injection. Sodium hydroxide or hydrochloric acid may be added to adjust pH to 5.0-7.0.

Distributed by:

INJECTAFER is manufactured under license from Vifor (International) Inc, Switzerland.

For more information go to www.injectafer.com or call 1-800-734-9236.

This Patient Information has been approved by the U.S. Food and Drug Administration.

Revised: 05/2023

PRINCIPAL DISPLAY PANEL - 2 ML CONTAINER LABEL

NDC 0517-0602-01
Rx Only
Injectafer® (ferric carboxymaltose injection)
100 mg/2 mL (50 mg/mL)
For Intravenous Use Only
Single Dose Vial. Discard Unused Portion.
AMERICAN REGENT, INC.
SHIRLEY, NY 11967

PRINCIPAL DISPLAY PANEL - 2 ML CARTON LABELING

NDC 0517-0602-01
Injectafer® (ferric carboxymaltose injection)
100 mg/2 mL (50 mg/mL)
For Intravenous Use Only
Single Dose Vial.
Discard Unused Portion.
Rx Only
AMERICAN REGENT, INC.
SHIRLEY, NY 11967

PRINCIPAL DISPLAY PANEL - 15 ML CONTAINER LABEL

NDC 0517-0650-01
Injectafer® (ferric carboxymaltose injection)
750 mg/15 mL(50 mg/mL)
FOR INTRAVENOUS USE ONLY
Single Dose Vial. Discard Unused Portion.
Rx Only
AMERICAN
REGENT, INC.
SHIRLEY, NY 11967

PRINCIPAL DISPLAY PANEL - 15 ML CARTON LABELING

NDC 0517-0650-01
Injectafer® (ferric carboxymaltose injection)
750 mg/15 mL (50 mg/mL)
FOR INTRAVENOUS USE ONLY
Single Dose Vial.
Discard Unused Portion.
Rx Only
AMERICAN
REGENT, INC.
SHIRLEY, NY 11967

PRINCIPAL DISPLAY PANEL - 20 ML CONTAINER LABEL

NDC 0517-0620-01
Rx Only
Injectafer® (ferric carboxymaltose injection)
1,000 mg/20 mL (50 mg/mL)
FOR INTRAVENOUS USE ONLY
Single-Dose Vial. Discard Unused Portion.
AMERICAN REGENT, INC.
SHIRLEY, NY 11967

PRINCIPAL DISPLAY PANEL - 20 ML CARTON LABELING

NDC 0517-0620-01

Injectafer® (ferric carboxymaltose injection)
1,000 mg/20 mL (50 mg/mL)
FOR INTRAVENOUS USE ONLY
Single-Dose Vial.
.
Discard Unused Portion.
Rx Only
AMERICAN
REGENT, INC.
SHIRLEY, NY 11967